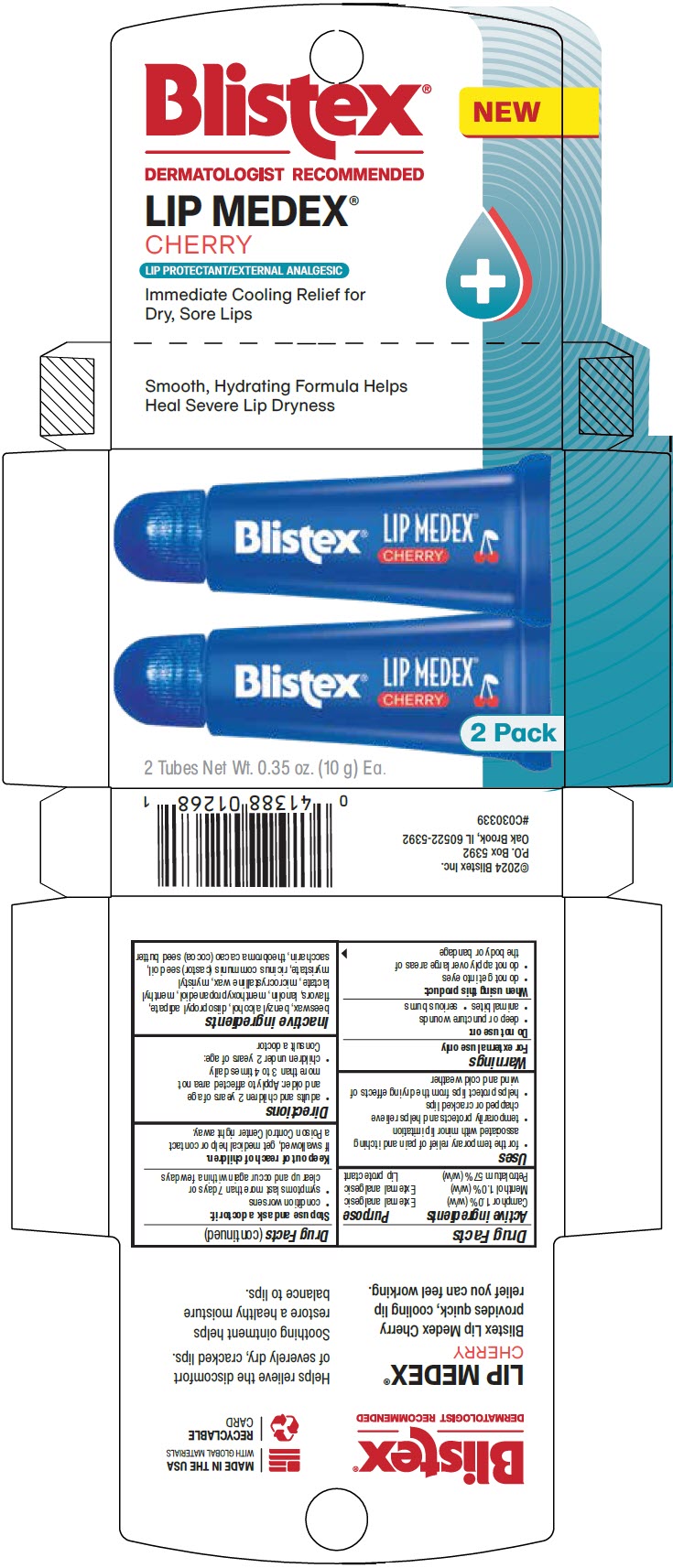 DRUG LABEL: Lip Medex Cherry
NDC: 10157-1199 | Form: OINTMENT
Manufacturer: Blistex Inc.
Category: otc | Type: HUMAN OTC DRUG LABEL
Date: 20240628

ACTIVE INGREDIENTS: PETROLATUM 57 g/100 g; CAMPHOR (SYNTHETIC) 1 g/100 g; MENTHOL, UNSPECIFIED FORM 1 g/100 g
INACTIVE INGREDIENTS: LANOLIN; MICROCRYSTALLINE WAX; COCOA BUTTER; YELLOW WAX; CASTOR OIL; MYRISTYL MYRISTATE; DIISOPROPYL ADIPATE; MENTHYL LACTATE, (-)-; BENZYL ALCOHOL; GLYCERIN METHYL ETHER; SACCHARIN

Lip Medex® Cherry

Drug Facts

ACTIVE INGREDIENT

Active ingredients | Purpose
Camphor 1.0% (w/w) | External analgesic
Menthol 1.0% (w/w) | External analgesic
Petrolatum 57% (w/w) | Lip protectant

Uses

- for the temporary relief of pain and itching associated with minor lip irritation
- temporarily protects and helps relieve chapped or cracked lips
- helps protect lips from the drying effects of wind and cold weather

Warnings

For external use only

Do not use on

- deep or puncture wounds
- animal bites
- serious burns

When using this product

- do not get into eyes
- do not apply over large areas of the body or bandage

Stop use and ask a doctor if

- condition worsens
- symptoms last more than 7 days or clear up and occur again within a few days

Keep out of reach of children.

If swallowed, get medical help or contact a Poison Control Center right away.

Directions

- adults and children 2 years of age and older: Apply to affected area not more than 3 to 4 times daily
- children under 2 years of age: Consult a doctor

Inactive ingredients

beeswax, benzyl alcohol, diisopropyl adipate, flavors, lanolin, menthoxypropanediol, menthyl lactate, microcrystalline wax, myristyl myristate, ricinus communis (castor) seed oil, saccharin, theobroma cacao (cocoa) seed butter

PRINCIPAL DISPLAY PANEL - 10 g Tube Carton

Blistex®

NEW

DERMATOLOGIST RECOMMENDED

LIP MEDEX®
CHERRY

LIP PROTECTANT/EXTERNAL ANALGESIC

Immediate Cooling Relief for
Dry, Sore Lips

Smooth, Hydrating Formula Helps
Heal Severe Lip Dryness

2 Pack

2 Tubes Net Wt. 0.35 oz. (10 g) Ea.